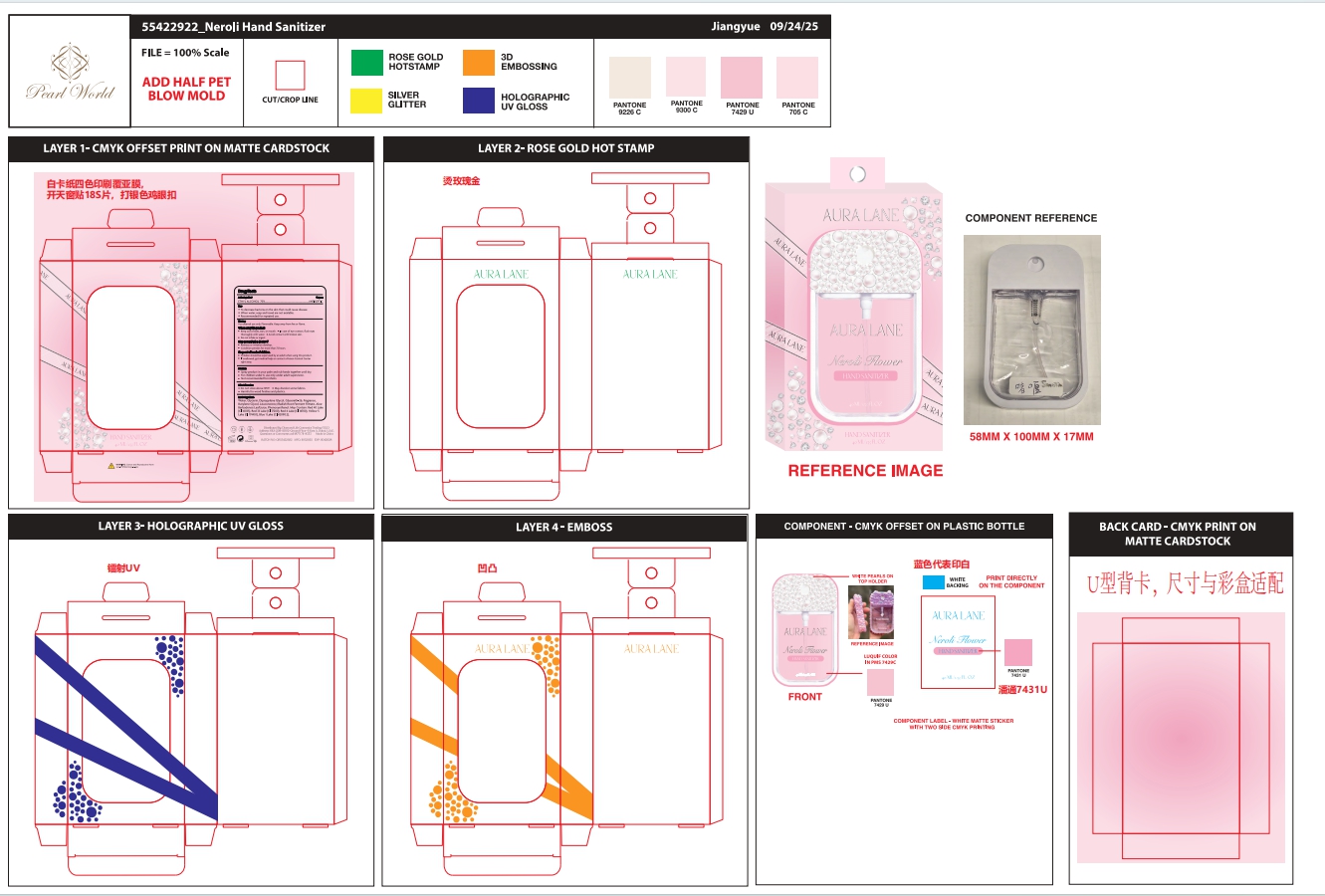 DRUG LABEL: Hand Sanitizer Mist
NDC: 85472-005 | Form: SPRAY
Manufacturer: ZHEJIANG GAORONG COSMETIC CO.,LTD.
Category: otc | Type: HUMAN OTC DRUG LABEL
Date: 20251121

ACTIVE INGREDIENTS: ALCOHOL 70 mL/100 mL
INACTIVE INGREDIENTS: WATER; DIPROPYLENE GLYCOL; GLYCERETH-26; GLYCERIN; RED 40 LAKE; LEUCONOSTOC/RADISH ROOT FERMENT FILTRATE; PHENOXYETHANOL; BUTYLENE GLYCOL; ALOE BARBADENSIS LEAF JUICE; BLUE 1 LAKE

ACTIVE INGREDIENT

ETHYL ALCOHOL 70%

PURPOSE

ANTISEPTIC

INDICATIONS AND USAGE

To decrease bacteria on the skin that could cause disease.
When water, soap and towel are not available.
Recommended for repeated use

WARNINGS

For external use only. Flammable. Keep away from fire or flame.

DO NOT USE

Redness of irritation develop.
Condition persists for more than 72 hours.

WHEN USING

Keep out of eyes, ears, or mouth.
In case of eye contact, flush eyes thoroughly with water.
Avoid contact with broken skin.
Do not inhale or ingest.

DOSAGE AND ADMINISTRATION

Spray product in your palm and rub hands together until dry.
For children under 6, use only under adult supervision.
Not recommended for infants.

STORAGE AND HANDLING

Do not store above 105°F.
May discolor some fabrics.
Harmful to wood finishes and plastics.

INACTIVE INGREDIENT

Water, Glycerin, Dipropylene Glycol, Glycereth-26, Fragrance, Butylene Glycol, Leuconostoc/Radish Root Ferment Filtrate, Aloe Barbadensis Leaf Juice, Phenoxyethanol.

May Contain:Red 40 Lake (CI 16035),Red 33 Lake (CI 17200),Red 4 Lake(CI 14700),Yellow 5 Lake(CI 19140:1),Blue 1 Lake (CI 42090:2).

KEEP OUT OF REACH OF CHILDREN

Children should be supervised by an adult when using this product.
lf swallowed, get medical help or contact a Poison Control Center right away.